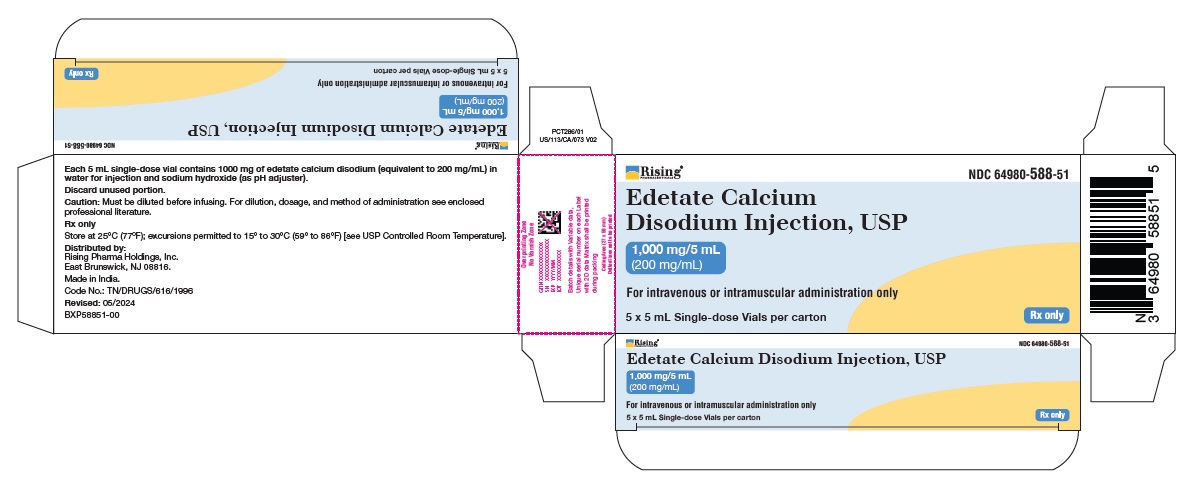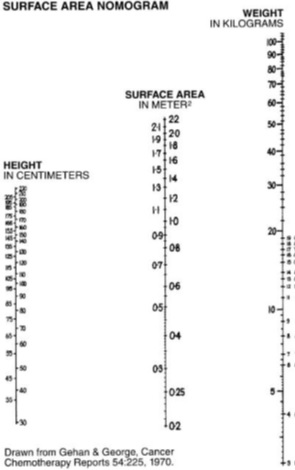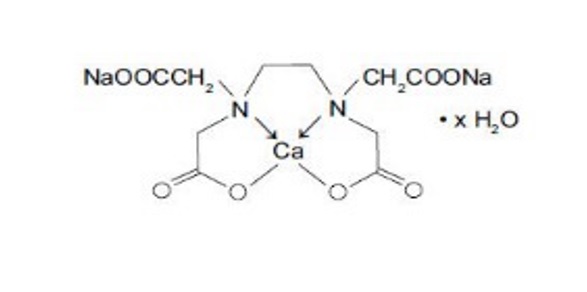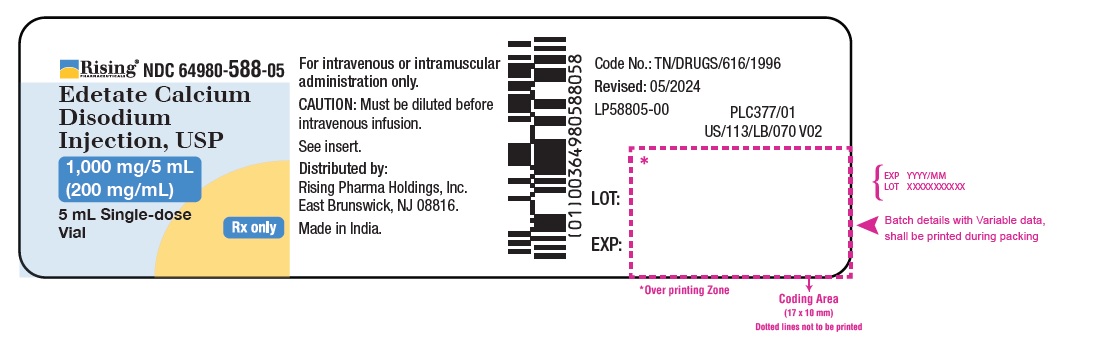 DRUG LABEL: Edetate Calcium Disodium
NDC: 64980-588 | Form: INJECTION
Manufacturer: Rising Pharma Holdings, Inc.
Category: prescription | Type: Human Prescription Drug Label
Date: 20250213

ACTIVE INGREDIENTS: EDETATE CALCIUM DISODIUM 200 mg/1 mL
INACTIVE INGREDIENTS: WATER; SODIUM HYDROXIDE

Edetate Calcium Disodium Injection, USP
For Intravenous and Intramuscular Use
Rx Only

WARNINGS

Edetate calcium disodium injection is capable of producing toxic effects which can be fatal. Lead encephalopathy is relatively rare in adults, but occurs more often in pediatric patients in whom it may be incipient and thus overlooked. The mortality rate in pediatric patients has been high. Patients with lead encephalopathy and cerebral edema may experience a lethal increase in intracranial pressure following intravenous infusion; the intramuscular route is preferred for these patients. In cases where the intravenous route is necessary, avoid rapid infusion. The dosage schedule should be followed and at no time should the recommended daily dose be exceeded.

DESCRIPTION

Edetate Calcium Disodium injection, USP is a sterile, injectable, chelating agent in concentrated solution for intravenous infusion or intramuscular injection. Each 5 mL single-dose vial contains 1,000 mg of edetate calcium disodium (equivalent to 200 mg/mL) in water for injection and sodium hydroxide (as pH adjuster). Chemically, this product is called [[N,N'-1,2-ethanediyl-bis[N-(carboxymethyl)-glycinato]](4-)-N,N',O,O',ON,ON']-, disodium, hydrate, (OC-6-21)-Calciate(2-).

Structural Formula:

C10 H12 CaN2 Na2 O8 • × H2 O

Molecular Weight: 374.27 (anhydrous)

CLINICAL PHARMACOLOGY

The pharmacologic effects of edetate calcium disodium are due to the formation of chelates with divalent and trivalent metals. A stable chelate will form with any metal that has the ability to displace calcium from the molecule, a feature shared by lead, zinc, cadmium, manganese, iron and mercury. The amounts of manganese and iron mobilized are not significant. Copper^1 is not mobilized and mercury is unavailable for chelation because it is too tightly bound to body ligands or it is stored in inaccessible body compartments. The excretion of calcium by the body is not increased following intravenous administration of edetate calcium disodium, but the excretion of zinc is considerably increased.^1
Edetate calcium disodium is poorly absorbed from the gastrointestinal tract. In blood, all the drug is found in the plasma. Edetate calcium disodium does not appear to penetrate cells; it is distributed primarily in the extracellular fluid with only about 5% of the plasma concentration found in spinal fluid.
The half-life of edetate calcium disodium is 20 to 60 minutes. It is excreted primarily by the kidney, with about 50% excreted in one hour and over 95% within 24 hours.^2 Almost none of the compound is metabolized.
The primary source of lead chelated by edetate calcium disodium is from bone; subsequently, soft-tissue lead is redistributed to bone when chelation is stopped.^3,4 There is also some reduction in kidney lead levels following chelation therapy.
It has been shown in animals that following a single dose of edetate calcium disodium urinary lead output increases, blood lead concentration decreases, but brain lead is significantly increased due to internal redistribution of lead (see WARNINGS).^5 These data are in agreement with the recent results of others in experimental animals showing that after a five day course of treatment there is no net reduction in brain lead.^6

INDICATIONS AND USAGE

Edetate calcium disodium is indicated for the reduction of blood levels and depot stores of lead in lead poisoning (acute and chronic) and lead encephalopathy, in both pediatric populations and adults.
Chelation therapy should not replace effective measures to eliminate or reduce further exposure to lead.

CONTRAINDICATIONS

Edetate calcium disodium should not be given during periods of anuria, nor to patients with active renal disease or hepatitis.

WARNINGS

See Boxed Warning.

PRECAUTIONS

General Precautions

Edetate calcium disodium may produce the same renal damage as lead poisoning, such as proteinuria and microscopic hematuria. Treatment-induced nephrotoxicity is dose-dependent and may be reduced by assuring adequate diuresis before therapy begins. Urine flow must be monitored throughout therapy which must be stopped if anuria or severe oliguria develop. The proximal tubule hydropic degeneration usually recovers upon cessation of therapy. Edetate calcium disodium must be used in reduced doses in patients with pre-existing mild renal disease. Patients should be monitored for cardiac rhythm irregularities and other ECG changes during intravenous therapy.

Information for patients

Patients should be instructed to immediately inform their physician if urine output stops for a period of 12 hours.

Laboratory tests

Urinalysis and urine sediment, renal and hepatic function and serum electrolyte levels should be checked before each course of therapy and then be monitored daily during therapy in severe cases, and in less serious cases after the second and fifth day of therapy. Therapy must be discontinued at the first sign of renal toxicity. The presence of large renal epithelial cells or increasing number of red blood cells in urinary sediment or greater proteinuria call for immediate stopping of edetate calcium disodium administration. Alkaline phosphatase values are frequently depressed (possibly due to decreased serum zinc levels), but return to normal within 48 hours after cessation of therapy. Elevated erythrocyte protoporphyrin levels (> 35 mcg/dL of whole blood) indicate the need to perform a venous blood lead determination. If the whole blood lead concentration is between 25 to 55 mcg/dL a mobilization test can be considered (see Diagnostic Test).^7,8 An elevation of urinary coproporphyrin (adults: > 250 mcg/day; pediatric patients under 80 lbs: > 75 mcg/day) and elevation of urinary delta aminolevulinic acid (ALA) (adults: > 4 mg/day; pediatric patients: > 3 mg/m^2/day) are associated with blood lead levels > 40 mcg/dL. Urinary coproporphyrin may be falsely negative in terminal patients and in severely iron-depleted pediatric patients who are not regenerating heme.^9 In growing pediatric patients long bone x-rays showing lead lines and abdominal x-rays showing radio-opaque material in the abdomen may be of help in estimating the level of exposure to lead.

Drug Interactions

There is no known drug interference with standard clinical laboratory tests. Steroids enhance the renal toxicity of edetate calcium disodium in animals.^7 Edetate calcium disodium interferes with the action of zinc insulin preparations by chelating the zinc.^7

Carcinogenesis, Mutagenesis, Impairment of Fertility

Long term animal studies have not been conducted with edetate calcium disodium to evaluate its carcinogenic potential, mutagenic potential or its effect on fertility.

Pregnancy

One reproduction study was performed in rats at doses up to 13 times the human dose and revealed no evidence of impaired fertility or harm to the fetus due to edetate calcium disodium.^10 Another reproduction study performed in rats at doses up to about 25 to 40 times the human dose revealed evidence of fetal malformations due to edetate calcium disodium, which were prevented by simultaneous supplementation of dietary zinc.^11 There are, however, no adequate and well-controlled studies in pregnant women. Because animal reproduction studies are not always predictive of human response, this drug should be used during pregnancy only if clearly needed.

Labor and Delivery

Edetate calcium disodium has no recognized use during labor and delivery, and its effects during these processes are unknown.

Nursing Mothers

It is not known whether this drug is excreted in human milk. Because many drugs are excreted in human milk, caution should be exercised when edetate calcium disodium is administered to a nursing woman.

Pediatric Use

Since lead poisoning occurs in pediatric populations and adults but is frequently more severe in pediatric patients, edetate calcium disodium is used in patients of all ages. The intramuscular route is preferred by some for young pediatric patients. In cases where the intravenous route is necessary, avoid rapid infusion (see WARNINGS). Urine flow must be monitored throughout therapy; Edetate Calcium Disodium therapy must be stopped if anuria or severe oliguria develops (see General Precautions). At no time should the recommended daily dosage be exceeded (see DOSAGE AND ADMINISTRATION).

ADVERSE REACTIONS

The following adverse effects have been associated with the use of edetate calcium disodium:

Body as a Whole: pain at intramuscular injection site, fever, chills, malaise, fatigue, myalgia, arthralgia.
Cardiovascular: hypotension, cardiac rhythm irregularities.
Renal: acute necrosis of proximal tubules (which may result in fatal nephrosis), infrequent changes in distal tubules and glomeruli.
Urinary: glycosuria, proteinuria, microscopic hematuria and large epithelial cells in urinary sediment.
Nervous System: tremors, headache, numbness, tingling.
Gastrointestinal: cheilosis, nausea, vomiting, anorexia, excessive thirst.
Hepatic: mild increases in SGOT and SGPT are common, and return to normal within 48 hours after cessation of therapy.
Immunogenic: histamine-like reactions (sneezing, nasal congestion, lacrimation), rash.
Hematopoietic: transient bone marrow depression, anemia.
Metabolic: zinc deficiency, hypercalcemia.

To report SUSPECTED ADVERSE REACTIONS, contact Rising Pharma Holdings, Inc. at 1-844-874-7464 or FDA at 1-800-FDA-1088 or www.fda.gov/medwatch.

OVERDOSAGE

Symptoms
Inadvertent administration of 5 times the recommended dose, infused intravenously over a 24 hour period, to an asymptomatic 16 month old patient with a blood lead content of 56 mcg/dL did not cause any ill effects. Edetate calcium disodium can aggravate the symptoms of severe lead poisoning, therefore, most toxic effects (cerebral edema, renal tubular necrosis) appear to be associated with lead poisoning. Because of cerebral edema, a therapeutic dose may be lethal to an adult or a pediatric patient with lead encephalopathy. Higher dosage of edetate calcium disodium may produce a more severe zinc deficiency.

Treatment
Cerebral edema should be treated with repeated doses of mannitol. Steroids enhance the renal toxicity of edetate calcium disodium in animals and, therefore, are no longer recommended.^7 Zinc levels must be monitored. Good urinary output must be maintained because diuresis will enhance drug elimination. It is not known if edetate calcium disodium is dialyzable.

DOSAGE AND ADMINISTRATION

When a source for the lead intoxication has been identified, the patient should be removed from the source, if possible. The recommended dose of edetate calcium disodium for asymptomatic adults and pediatric patients whose blood lead level is < 70 mcg/dL but > 20 mcg/dL (World Health Organization recommended upper allowable level) is 1,000 mg/m^2/day whether given via intravenous infusion or intramuscularly (see Surface Area Nomogram).

For adults with lead nephropathy, the following dosing regimen has been suggested: 500 mg/m^2 every 24 hours for 5 days for patients with serum creatinine levels of 2 to 3 mg/dL, every 48 hours for 3 doses for patients with creatinine levels of 3 to 4 mg/dL, and once weekly for patients with creatinine levels above 4 mg/dL. These regimens may be repeated at one month intervals.^12

Edetate calcium disodium, used alone, may aggravate symptoms in patients with very high blood lead levels. When the blood lead level is > 70 mcg/dL or clinical symptoms consistent with lead poisoning are present, it is recommended that edetate calcium disodium be used in conjunction with BAL (dimercaprol). Please consult published protocols and specialized references for dosage recommendations of combination therapy.^14-18
Therapy of lead poisoning in adults and pediatric patients with edetate calcium disodium is continued over a period of five days. Therapy is then interrupted for 2 to 4 days to allow redistribution of the lead and to prevent severe depletion of zinc and other essential metals. Two courses of treatment are usually employed; however, it depends on the severity of the lead toxicity and the patient's tolerance of the drug.
Edetate calcium disodium is equally effective whether administered intravenously or intramuscularly. The intramuscular route is used for all patients with overt lead encephalopathy and this route is preferred by some for young pediatric patients.
Acutely ill individuals may be dehydrated from vomiting. Since edetate calcium disodium is excreted almost exclusively in the urine, it is very important to establish urine flow with intravenous fluid administration before the first dose of the chelating agent is given; however, excessive fluid must be avoided in patients with encephalopathy. Once urine flow is established, further intravenous fluid is restricted to basal water and electrolyte requirements. Administration of edetate calcium disodium should be stopped whenever there is cessation of urine flow in order to avoid unduly high tissue levels of the drug. Edetate calcium disodium must be used in reduced doses in patients with pre-existing mild renal disease.

Intravenous Administration

Add the total daily dose of edetate calcium disodium (1,000 mg/m^2/day) to 250 to 500 mL of 5% dextrose or 0.9% sodium chloride injection. The total daily dose should be infused over a period of 8 to 12 hours. Discard unused portion. Edetate calcium disodium injection is incompatible with 10% dextrose, 10% invert sugar in 0.9% sodium chloride, lactate Ringer's, Ringer's, one-sixth molar sodium lactate injections, and with injectable amphotericin B and hydralazine hydrochloride.

Intramuscular Administration

The total daily dosage (1,000 mg/m^2/day) should be divided into equal doses spaced 8 to 12 hours apart. Discard unused portion. Lidocaine or procaine should be added to the edetate calcium disodium injection to minimize pain at the injection site. The final lidocaine or procaine concentration of 5 mg/mL (0.5%) can be obtained as follows: 0.25 mL of 10% lidocaine solution per 5 mL concentrated edetate calcium disodium; 1 mL of 1% lidocaine or procaine solution per mL of concentrated edetate calcium disodium. When used alone, regardless of method of administration, edetate calcium disodium should not be given at doses larger than those recommended.

Diagnostic Test

Several methods have been described for lead mobilization tests using edetate calcium disodium to assess body stores.^(7, 9,12,13,18)
These procedures have advantages and disadvantages that should be reviewed in current references. Edetate calcium disodium mobilization tests should not be performed in symptomatic patients and in patients with blood lead levels above 55 mcg/dL for whom appropriate therapy is indicated.
Parenteral drugs should be inspected visually for particulate matter and discoloration prior to administration, whenever solution and container permit.

HOW SUPPLIED

Edetate Calcium Disodium injection, USP 5 mL single-dose vial (NDC 64980-588-05) containing 200 mg of edetate calcium disodium per mL (1,000 mg per vial), in boxes containing 5 vials (NDC 64980-588-51).

Store at 25°C (77°F); excursions permitted to 15° to 30°C (59° to 86°F) [see USP Controlled Room Temperature].

REFERENCES

1. Thomas DJ, Chisolm JJ. Lead, zinc and copper decorporation during calcium disodium ethylene diamine tetraacetate treatment of lead-poisoned children. J Pharmacol Exp Therapeu. 1986; 239: 829–835.
2. The Pharmacological Basis of Therapeutics, 7th edition, Goodman and Gilman, editors. MacMillan Publishing Company, New York, 1985, pp. 1619–1622.
3. Hammond PB, Aronson AL, Olson WC. The mechanism of mobilization of lead by ethylenediaminetetraacetate. J Pharmacol Exp Therapeu. 1967; 157: 196–206.
4. Van deVyver FL, D'Haese PC, Visser WJ, et al. Bone lead in dialysis patients. Kidney Intl. 1988; 33: 601–607.
5. Cory-Slecta DA, Weiss B, Cox C. Mobilization and redistribution of lead over the course of calcium disodium ethylene diamine tetraacetate chelation therapy. J Pharmacol Exp Therapeu. 1987; 243: 804–813.
6. Chisolm JJ. Mobilization of lead by calcium disodium edetate. Am J Dis Child. 1987;141: 1256–1257.
7. Drug Evaluations, 6th edition, American Medical Association, Saunders, Philadelphia, 1986, pp. 1637–1639.
8. Centers for Disease Control: Preventing lead poisoning in young children. Atlanta, GA, Department of Health and Human Services, 1985 Jan.
9. Finberg L, Rajagopal V. Diagnosis and treatment of lead poisoning in children. J Family Med. 1985 April: 3–12.
10. Schardein JL, Sakowski R, Petrere J, et al. Teratogenesis studies with EDTA and its salts in rats. Toxicol Appl Pharmacol. 1981; 61: 423–428.
11. Swenerton H, Hurley LS. Teratogenic effects of a chelating agent and their prevention by zinc. Science. 1971; 173: 62–64.
12. American Hospital Formulary Service, Drug Information, 1988, pp. 1695–1698.
13. Markowitz ME, Rosen JF. Assessment of lead stores in children: Validation of an 8-hour CaNa2EDTA (Edetate Calcium Disodium) provocative test. J Pediatrics. 1984;104: 337–341.
14. Piomelli S, Rosen JF, Chisolm JJ, et al. Management of childhood lead poisoning. J Pediatrics. 1984; 105: 523–532.
15. Sachs HK, Blanksma LA, Murray EF, et al. Ambulatory treatment of lead poisoning: Report of 1,155 cases. Pediatrics. 1970; 46: 389.
16. Chisolm JJ. The use of chelating agents in the treatment of acute and chronic lead intoxication in childhood. J Pediatrics. 1968; 73: 1.
17. Coffin R, Phillips JL, Staples WI, et al. Treatment of lead encephalopathy in children. J Pediatrics. 1966; 69: 198–206.
18. Chisolm JJ. Increased lead absorption and acute lead poisoning. Current Pediatric Therapy 12, Gillis and Kagan, editors, WB Saunders, Philadelphia, 1986, pp. 667–671.

Distributed by:
Rising Pharma Holdings, Inc.
East Brunswick, NJ 08816.
Made in India
Code No.: TN/DRUGS/616/1996
Revised: 01/2025
PIP58851-01

PACKAGE LABEL.PRINCIPAL DISPLAY PANEL

PRINCIPAL DISPLAY PANEL - 5 mL Single-dose Vial

Rising Pharma Holdings, Inc.

Edetate Calcium Disodium Injection, USP

1000 mg/5 mL (200 mg/mL)

NDC 64980-588-05

Rx only

NDC 64980-588-51

5 x 5 mL Single-dose Vials per carton

For intravenous or intramuscular administration only

Rx Only